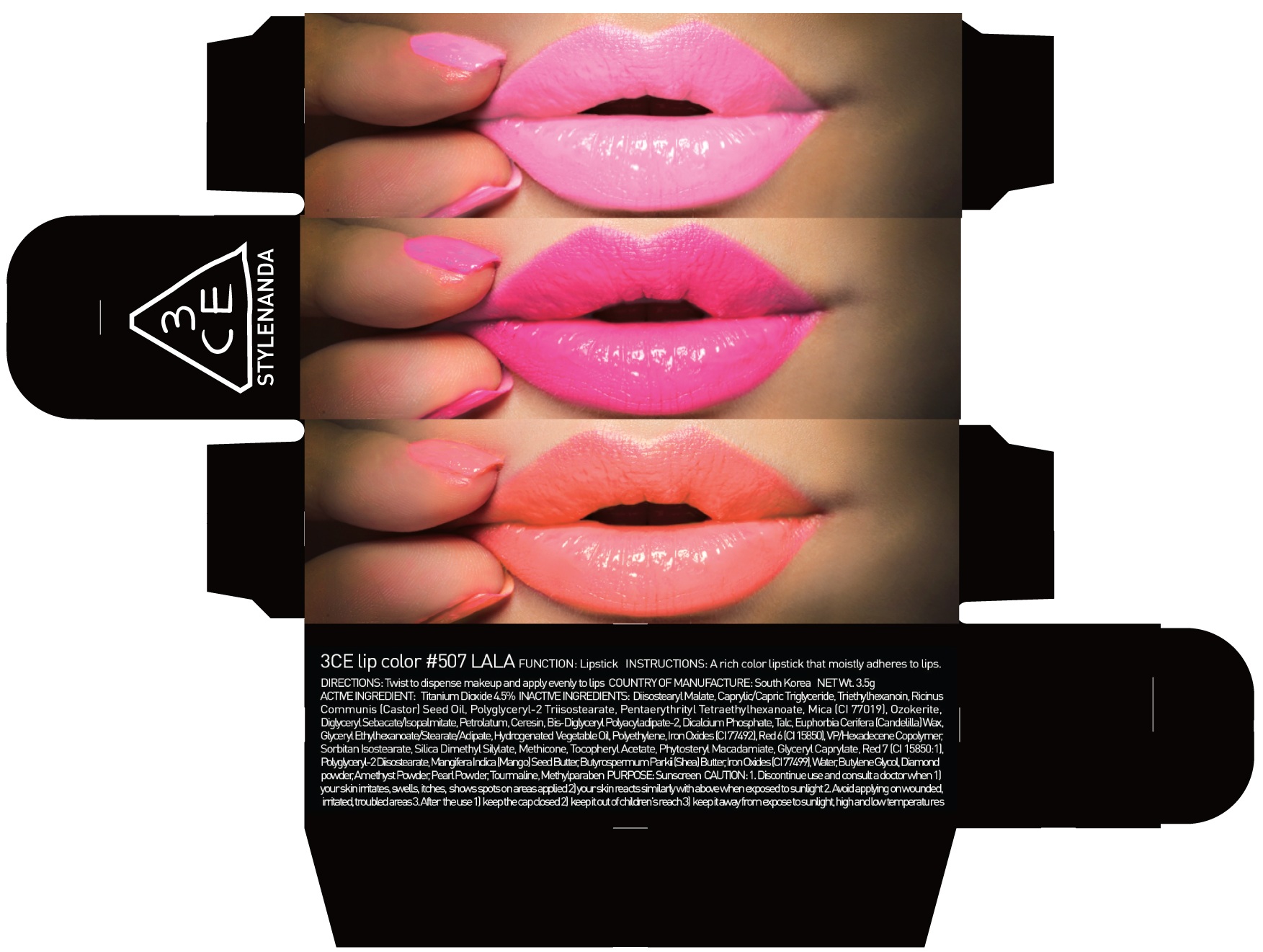 DRUG LABEL: 3CE LIP COLOR 507 LALA
NDC: 60764-076 | Form: LIPSTICK
Manufacturer: Nanda Co., Ltd
Category: otc | Type: HUMAN OTC DRUG LABEL
Date: 20161007

ACTIVE INGREDIENTS: Titanium Dioxide 0.15 g/3.5 g
INACTIVE INGREDIENTS: Diisostearyl Malate; Triethylhexanoin

ACTIVE INGREDIENT

Active Ingredient: Titanium Dioxide 4.5%

INACTIVE INGREDIENT

Inactive Ingredients: Diisostearyl Malate, Caprylic/Capric Triglyceride, Triethylhexanoin, RicinusCommunis (Castor) Seed Oil, Polyglyceryl-2 Triisostearate, PentaerythritylTetraethylhexanoate, Mica (CI 77019), Ozokerite, DiglycerylSebacate/Isopalmitate, Petrolatum, Ceresin, Bis-Diglyceryl Polyacyladipate-2, Dicalcium Phosphate, Talc, Euphorbia Cerifera (Candelilla) Wax, Glyceryl Ethylhexanoate/Stearate/Adipate, Hydrogenated Vegetable Oil, Polyethylene, Iron Oxides (CI 77492), Red 6 (CI 15850), VP/Hexadecene Copolymer, SorbitanIsostearate, Silica Dimethyl Silylate, Methicone, Tocopheryl Acetate, PhytosterylMacadamiate, Glyceryl Caprylate, Red 7 (CI 15850:1), Polyglyceryl-2 Diisostearate, MangiferaIndica (Mango) Seed Butter, ButyrospermumParkii (Shea) Butter, Iron Oxides (CI 77499), Water, Butylene Glycol, Diamond powder, Amethyst Powder, Pearl Powder, Tourmaline, Methylparaben

PURPOSE

Purpose: Sunscreen

CAUTION

CAUTION: 1. Discontinue use and consult a doctor when - your skin irritates, swells, itches, shows spots on areas applied - your skin reacts similarly with above when exposed to sunlight 2. Avoid applying on wounded, irritated, troubled areas 3. After the use - keep the cap closed - keep it out of children's reach - keep it away from expose to sunlight, high and low temperatures

DESCRIPTION

INSTRUCTIONS: A rich color lipstick that moistly adheres to lips.

Directions: Twist to dispense makeup and apply evenly to lips